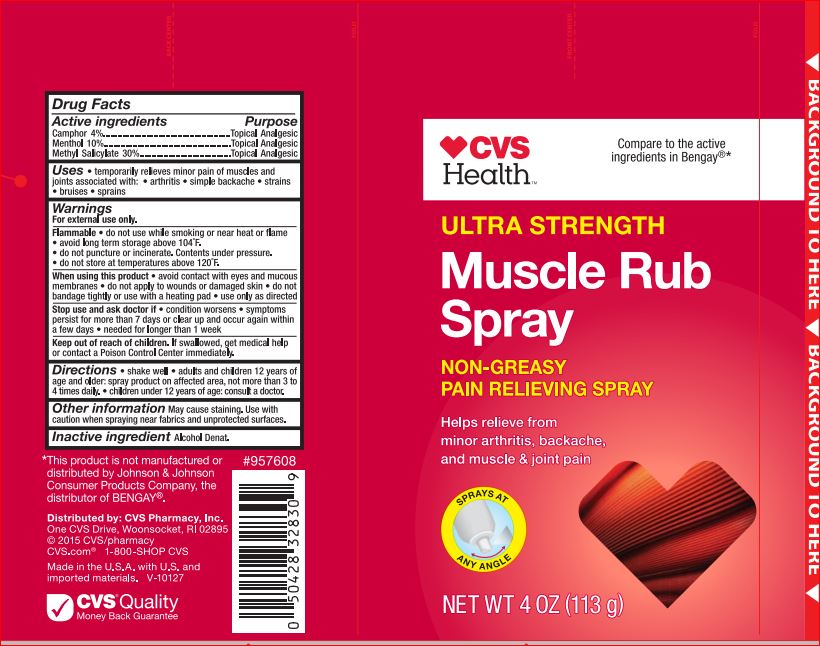 DRUG LABEL: Muscle Rub Ultra Strength
NDC: 59779-492 | Form: SPRAY
Manufacturer: CVS
Category: otc | Type: HUMAN OTC DRUG LABEL
Date: 20171201

ACTIVE INGREDIENTS: CAMPHOR (SYNTHETIC) 4 g/100 g; Menthol 10 g/100 g; Methyl Salicylate 30 g/100 g
INACTIVE INGREDIENTS: ALCOHOL

Drug Facts

Active Ingredients Purpose

Camphor – 4.00% Topical Analgesic
Menthol – 10.00% Topical Analgesic
Methyl Salicylate - 30% Topical Analgesic

Warning For external use only

Flammable.

• do not use while smoking or near heat or flame
• avoid long term storage above 104oF
• do not puncture or incinerate. Contents under pressure
• do not store at temperature above 120oF

When using this product

• avoid contact with eyes and mucous membranes
• do not apply to wounds or damages skin
• do not bandage tightly or use with a heating pad
• use only as directed

Stop use and ask a doctor if

• condition worsens
• symptoms last more than 7 days or clear up and occur again within a few days
• needed for longer than 1 week

Keep out of reach of the children

If product is swallowed, get medical help or contact a Poison Control Center right away

Uses

temporarily reliefs minor pain associated with • arthritis • simple backache •muscle strains • bruises • muscle sprains

Directions

• shake well
• adults and children 12 years of age and older: spray on affected area, not more than 3 to 4 times daily
• children under 12 years of age: consult a doctor

Inactive Ingredient

Alcohol Denat.